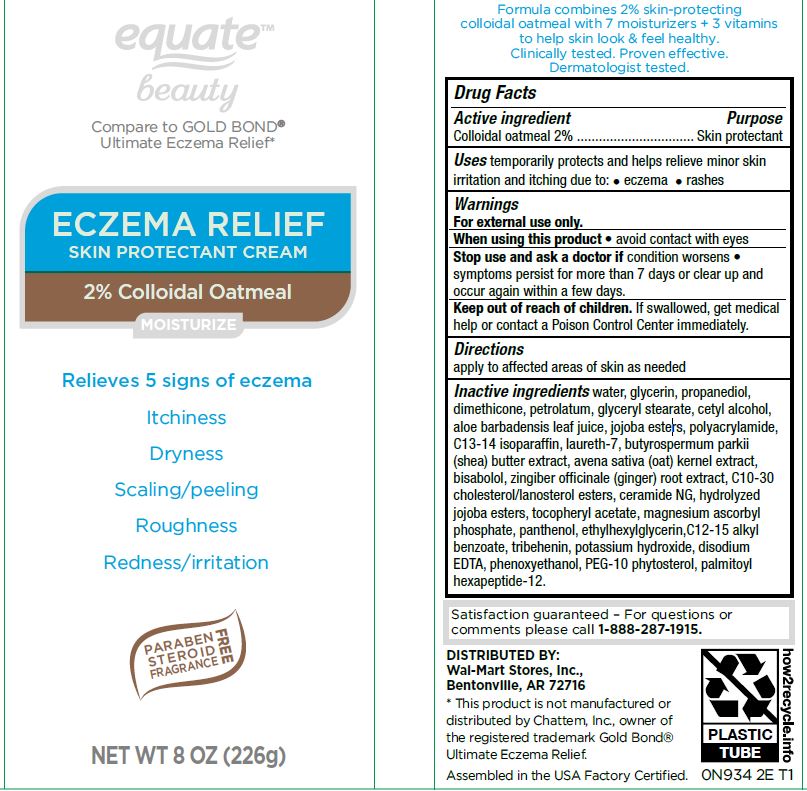 DRUG LABEL: Eczema Reliegf Skin Protectant
NDC: 79903-209 | Form: CREAM
Manufacturer: Walmart
Category: otc | Type: HUMAN OTC DRUG LABEL
Date: 20260120

ACTIVE INGREDIENTS: OATMEAL 2 g/100 g
INACTIVE INGREDIENTS: GLYCERIN; PROPANEDIOL; DIMETHICONE; PETROLATUM; GLYCERYL STEARATE CITRATE; CETYL ALCOHOL; ALOE; HYDROGENATED JOJOBA OIL, RANDOMIZED; POLYACRYLAMIDE (1500 MW); C13-14 ISOPARAFFIN; LAURETH-7; SHEA BUTTER; OAT; LEVOMENOL; GINGER; C10-30 CHOLESTEROL/LANOSTEROL ESTERS; CERAMIDE NG; .ALPHA.-TOCOPHEROL ACETATE; MAGNESIUM ASCORBYL PHOSPHATE; PANTHENOL; ETHYLHEXYLGLYCERIN; ALKYL (C12-15) BENZOATE; TRIBEHENIN; POTASSIUM HYDROXIDE; EDETATE DISODIUM ANHYDROUS; PHENOXYETHANOL

Eczema Reliegf Skin Protectant Cream PLSF-1857

Active ingredient Purpose

Colloidal oatmeal 2% .......................... Skin protectant

Uses

temporarily protects and helps relieve minor skin irritation and itching due to: • eczema • rashes

When using this product

• avoid contact with eyes

Stop use and ask a doctor if

condition worsens • symptoms persist for more than 7 days or clear up and occur again within a few days.

Keep out of reach of children.

If swallowed, get medical help or contact a Poison Control Center immediately.

Directions

apply to affected areas of skin as needed

Inactive ingredients

Water,

glycerin
propanediol
dimethicone
petrolatum
glyceryl stearate
cetyl alcohol
aloe barbadensis leaf juice
jojoba esters
polyacrylamide
C13-14 isoparaffin
laureth-7
butyrospermum parkii (shea) butter extract
avena sativa (oat) kernel extract
bisabolol
zingiber officinale (ginger) root extract
C10-30 cholesterol/lanosterol esters
ceramide NG
hydrolyzed jojoba esters
tocopheryl acetate
magnesium ascorbyl phosphate
panthenol
ethylhexylglycerin
C12-15 alkyl benzoate
tribehenin
potassium hydroxide
disodium EDTA
phenoxyethanol
PEG-10 phytosterol